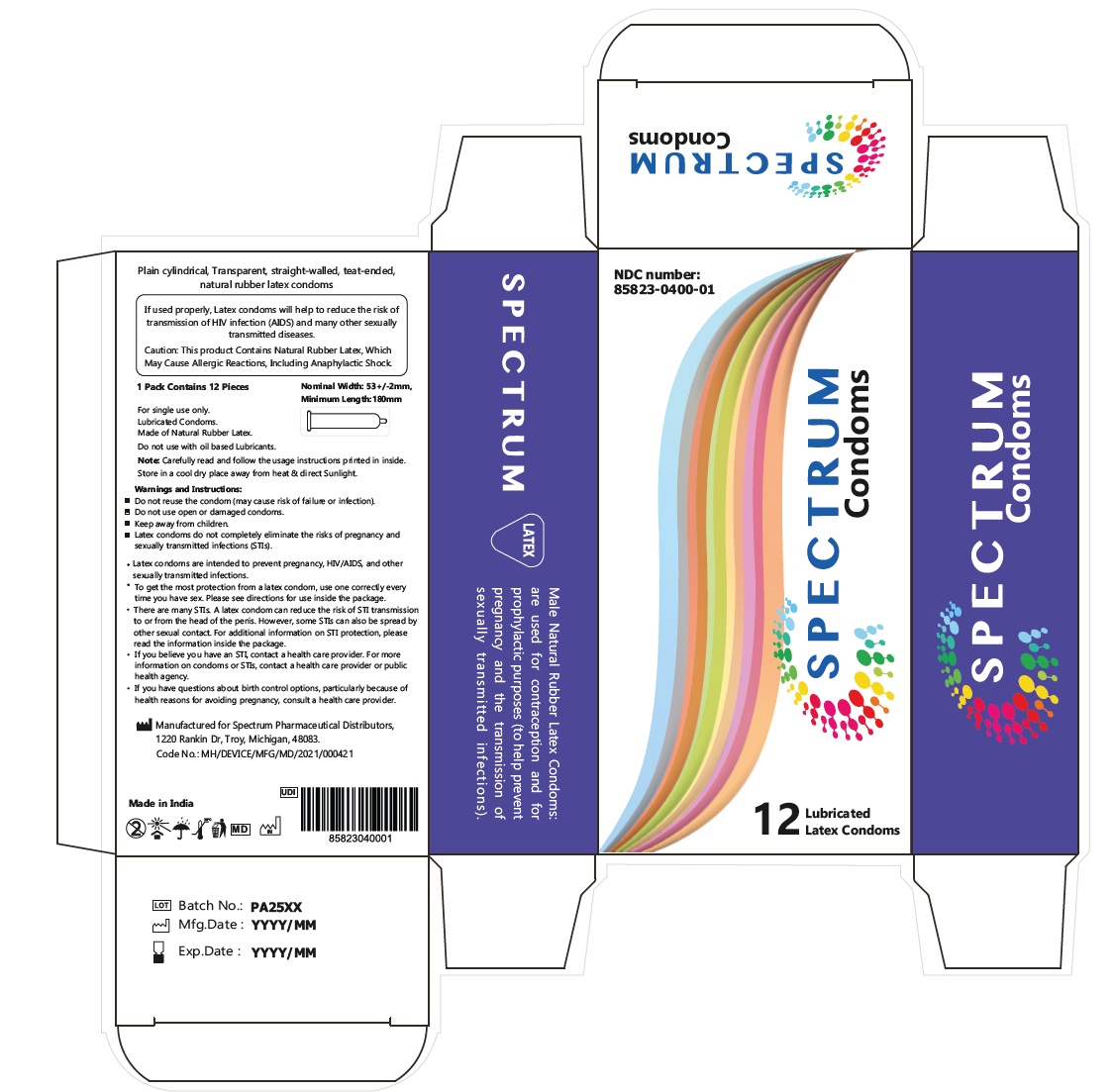 DRUG LABEL: SPECTRUM CONDOM 53mm MC
NDC: 85823-400
Manufacturer: Spectrum Pharmaceutical Distributors
Category: other | Type: OTC MEDICAL DEVICE LABEL
Date: 20251030

SPECTRUM CONDOM 53mm MC

SPECTRUM CONDOM 53mm MC

DIRECTIONS FOR USE BIRTH CONTROL GUIDE

Male Natural Rubber Latex Condoms

BEFORE INTERCOURSE
1. Carefully open the package so the condom does not tear. Do not unroll the condom before

CUPID Brand Male Natural Rubber Latex Condoms: are used for contraception and or prophylactic purposes (or help prevent pregnancy and the transmission of sexually transmitted infections).

1. Use a new condom for each act of sex.

If you do not want to get pregnant, there are many birth control options to choose from. Noone product is best for everyone. Some methods are more eﬀective than others at preventng pregnancy.Check the pregnancy rates on this chart to get an idea of how eﬀectve the product is at preventng pregnancy.

FDA-Approved Methods

Number of pregnancies expected (per 100 women)*

Use Some Risks or Side Effects* This chart does not list all of the risks and side effects for each product putng it on.

2. If you are not circumcised, pull back the foreskin. Put the condom on the end of the hard penis.
Note: If the condom is initally placed on the penis backwards, do not turn it around. Throw it

2. Tear open the package carefully. Do not use ﬁngernails, teeth, or anything that can damage the condom.

3. Before any sexual contact, place the condom on the head of the erect penis with the rolled side

The pregnancy rates tell you the number of pregnancies expected per 100 women during the ﬁrst year of typical use. Typical use shows how eﬀectve the diﬀerent methods are during actual use (including sometmes using a method in a way that is not correct or Patch 9 Put on a new patch each week for 3 weeks (21 total Spotting/bleeding between periods Nausea, Breast tenderness, Headache away and start with a new one.

3. Pinching the tp of the condom to squeeze out air, roll on the condom untl it reaches the base of the penis. Place the condom on the erect penis before any contact occurs between the penis and the out. Lesions, pre-ejaculate secretons, semen, vaginal secretons and blood can all transmit infectous oganisms.

4. Unroll or pull the condom all the way to the base of the erect penis. If the condom doesn’t not consistent). The only sure way to avoid pregnancy is not to have any sexual contact. Talk to your health care provider about the best method for you, days).Don't put on a Skin Irritation patch during the fourth week partner’s body to assist in the preventon of sexually transmited infecton and pregnancy.

4. Check to make sure there is space at the tp and that the condom is not boken. With the condom unroll easily, it may be on backwards, damaged or too old. Throw it away and start over with a new condom.

FDA-Approved

Number of Use Some Risks or Side Effects*

Vaginal Contraceptive Ring

9 Put the ring into the vagina yourself.

Vaginal discharge, discomfort in the vagina, mild irritation. on, insert the penis for intercourse.

AFTER INTERCOURSE
5. When withdrawing the penis after sex and soon after ejaculation, hold the rim of the condom to

5. Immediately after ejaculation, hold the rim of the condom in place and withdraw the penis while it is stll erect. Avoid spilling semen.
6. Dispose of a used condom by wrapping it in tssue and thowing it into the trash. Wash your hands with soap and water.Methods

pregnancies expected (per 100 women)*

This chart does not list all of the risks and side effects for each product Diaphragm with Keep the ring in your Headache, Nausea, Mood vagina for 3 weeks & changes, Breast tenderness then take it out for one week.

keep the condom in place.
6.Remove the condom while the penis is stll hard. Be careful not to spill any semen on the woman’s genitals.

DISPOSAL OF THE CONDOM

7. If you have questons about birth control optons, partcularly because of health reasons for avoiding pregnancy, consult a health care provider.
Precautions:

Sterilization Surgery for Women
Sterilization Surgery

Less than - 1 Onetime Permanent.
Less than - 1 Onetime

Pain ,Bleeding, Infection or other complications after surgery Pain ,Bleeding, Infection Sponge with Spermicide

12 Must use every time you have sex
12-24 Must use every time you have sex

Irritation, Allergic reactions Urinary tract infection Irritation

Wrap the used condom in a piece of paper and throw it away safely where children cannot get hold of

Do not reuse latex condoms.
Store latex condoms in a cool, dry place (below 30ºC) and avoid exposure to direct for Men procedure Permanent.

Cervical Cap with Spermicide

17-23

Must use every time you have sex

Irritation, Allergic reactions Abnormal Pap test it. Dispose in a closed rubbish bin, burry or burn. It may be disposed by throwing in a pit

latrine. Do not throw it in a ﬂushing toilet.

WARNING! Use the condom only once. The Condom is made of Natural Rubber Latex, which might sunlight.

If the rubber material is sticky or brittle or obviously damaged, do not use the condom. If the color is uneven or changed, do not use the condom.

IUD Copper Less than - 1 Inserted by a healthcare provider. Lasts up to 10 years.

cramps, Heavier, Longer periods Spotting between periods Male Condom 18

Must use every time Irritation, Allergic reactions you have sex.
Provide Protection against some STIs.

cause allergic reactions including anaphylactic shock. Try to keep condoms in a cool, dry place. Do Make sure there is adequate lubrication. If you add lubricant, use a water-based lubricant.

IUD with Progestin Less than - 1 Inserted by a Irregular bleeding No periods

Female Condom 21 Must use every time Discomfort or pain not leave them in the sun or carry them in a wallet or back pocket under fricton for a long time.

Consult a doctor or pharmacist about the compatibility of topical medicines that might come in contact with the condom.

INSPECTING AND OPENING THE PACKET

[Manufacturers may identify one or more examples.] DO NOT USE OIL-BASED LUBRICANTS, such as those
made with petroleum jelly (e.g., Vaseline®), mineral oil, vegetable oil, or cold cream, as these may damage the condom.

healthcare provider. Lasts up to 3-5 years, depending on type Implantable Rod Less than - 1 Inserted by a (amenorrhea) Abdominal /pelvic pain

Menstrual Changes Weight gain Spermicide Alone you have sex. Provide Protection against some STIs.28 Must use every during insertion or sex Burning Sensation, rash or itching Irritation, Allergic reactions Before sex, talk to your partner about using a condom. Do not use a condom that has expired. Check Degree of STI Protection healthcare provider. Acne time you have sex Urinary tract infection the expiry date on the package. Do not use a condom if the packaging is torn or damaged, if the condom is sticky or dried out, or if the color has changed. Discard that condom and use a new one from an undamaged package. Open the packet and handle condoms carefully to avoid damage to the condom by ﬁngernails, jewelry, etc. Do not worry if you ﬁnd a slippery substance in and on the Latex condoms reduce the risk of transmitting STIs by providing a barrier against the source of the infection.

Latex condoms are most effective against STIs such as HIV infection (AIDS) and gonorrhea Lasts up to 3 years.

Shot/Injection 6 Need a shot every 3 months Mood swings or depressed mood Headache Loss of bone density. Irregular bleeding/

OTHER CONTRACEPTION
Emergency Contraceptives (EC): May be used if you did not use birth control or if your regular birth control fails (such as a condom breaks). It should no be used as a regular form of birth control. Emergency control. Emergency contraception prevents about 55-85% of predicated
pregnancies.

condom when opening the packet. Some condoms have a lubricant to make sex smoother.

LUBRICATION

that are spread by contact with the head of the penis.
Latex condoms are less effective against STIs such as Human Papillomavirus (HPV) and herpes.

bleeding between periods Headaches, Weight gain, Nervousness, Dizziness, Levonorgestrel 1.5mg (1 pill) 7 out of every 8 women who would have gotten Swallow the pills as soon as possible Menstrual changes Headache Lower stomach (abdominal) pain Nausea, Vomiting, 1-Lubricaton is very important. The condom covered penis should slide easily in the partner’s body.

These STIs can also be spread by contact with infected skin that is not covered by the condom.

Abdominal discomfort

Levonorgestrel .75mg pregnant will no become within 3 days after Dizziness Tiredness Otherwise the condom may cause pain or may make the body more vulnerable to HIV, or may break.

If you believe you have an STI, contact a health care provider. For more information on latex Oral Contraceptives 9 Must swallow a Spotting/bleeding between (2 pill) pregnant after taking this EC. having unprotected sex

Breast pain

2-Use only water-based lubricants, such as water, water-based lubricant, or spermicidal foam.
3-Do not use lubricants with oil in them, such as petroleum jelly, body lotions, baby oil, butter condoms or STIs, contact a health care provider or a public health agency.“ The Pill” (Combined Pill) pill every day.

periods Nausea, Breast tenderness, Headache Ulipristal Acetate 6 or 7 out of every 10 Swallow the pills women who would have within 5 days after Headache Nausea Abdominal Pain Menstrual pain mineral oil or cooking oil. Oil weakens latex condoms.

STANDARD

1 2 3 4

gotten pregnant will not having unprotected

Tiredness

Dizziness

4-Do not put anything into the vagina to make it drier.
IN CASE OF SLIPPING OR BREAKING

The Male Latex Condoms are produced based on ISO 4074 and WHO/UNFPA Male Latex Oral Contraceptives “The Pill”(Extended Continuous Use

9 Must swallow a pill every day. Spotting/bleeding between periods Nausea, Breast tenderness, Headache become pregnant after taking this EC.

sex.

1- If you feel the condom might be slipping, check it with your hand. It is very important that the condom does not slip oﬀ during Sex
2-If the condom breaks, stop sex at once. Remove the torn condom and put on another.
3-If the condom breaks or leaks and the man has ejaculated, take acton to prevent pregnancy. Go to the nearest clinic for emergency contraception as soon as possible, within 72 hours of the breakage/leakage.

Condom Technical Speciﬁcaton.
5 6 7

Date of Issue: 23/05/2022

Combined Pill) Oral Contraceptives “ The Mini Pill” (Progestin Only)

9 Must swallow a pill at the same time every day.

Spotting/bleeding between periods Nausea, Breast tenderness, Headache

* For more information on the chance of getting pregnant while using a method or on the risks of a
specific product, please check the product label or Trussell, J (2011). ”Contraceptive failure in
the United States.” Contraception 83(5):397-404

Principal Display Panel

Male Natural Rubber Latex Condoms

1 pack contains 12 pieces